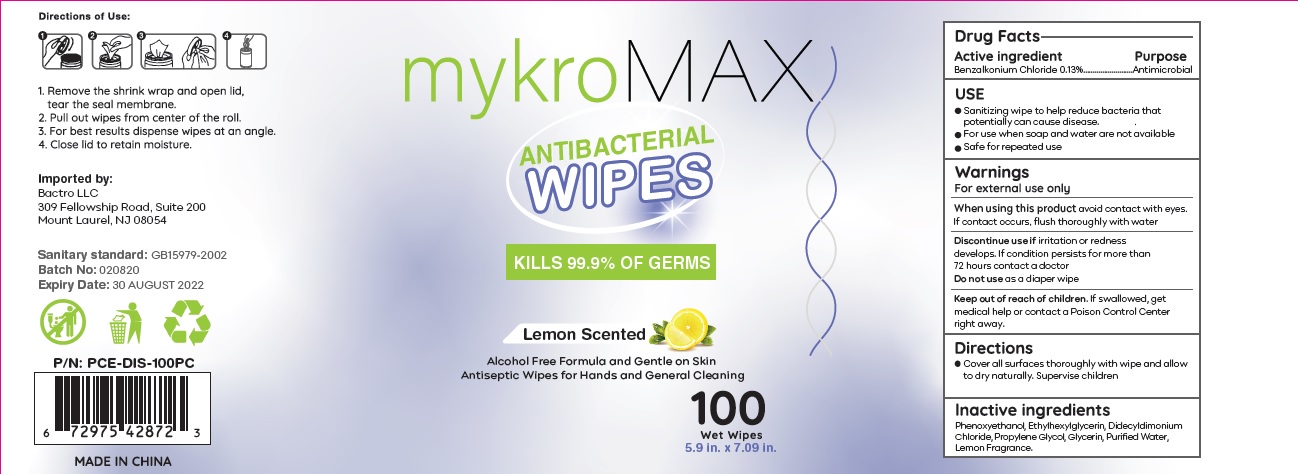 DRUG LABEL: Mykro Max Antibacterial wipes
NDC: 71734-323 | Form: SWAB
Manufacturer: JIANGMEN SHUIZIRUN SANITARY ARTICLES CO., LTD.
Category: otc | Type: HUMAN OTC DRUG LABEL
Date: 20200813

ACTIVE INGREDIENTS: benzalkonium chloride 0.13 g/100 g
INACTIVE INGREDIENTS: water; PHENOXYETHANOL; ETHYLHEXYLGLYCERIN; PROPYLENE GLYCOL; GLYCERIN

DRUG FACTS

Active Ingredient

Benzalkonium Chloride .......... 0.13 %

Purpose

Antiseptic

Uses:

- Sanitizing wipe to help reduce bacteria that potentially can cause disease.
- For use when soap and water are not available.
- Safe for repeated use.

Warnings

For external use only.

When using this product avoid contact with eyes. If contact occurs, flush thoroughly with water.

Discontinue use if irritation or redness develops. If condition persists for more than 72 hours contact a doctor.

Do not useas a diaper wipe

Keep out of reach of children.

if swallowed get medical help or contact a Poison Control Center right away.

Directions

- Cover all surfaces thoroughlly with wipe and allow to dry naturally. Supervise children.

Inactive Ingredients:

Phenoxyethanol, Ethylhexylglycerin, Didecyldimonium Chloride, Propylene Glycol, Glycerin, Purified Water, Lemon Fragrance